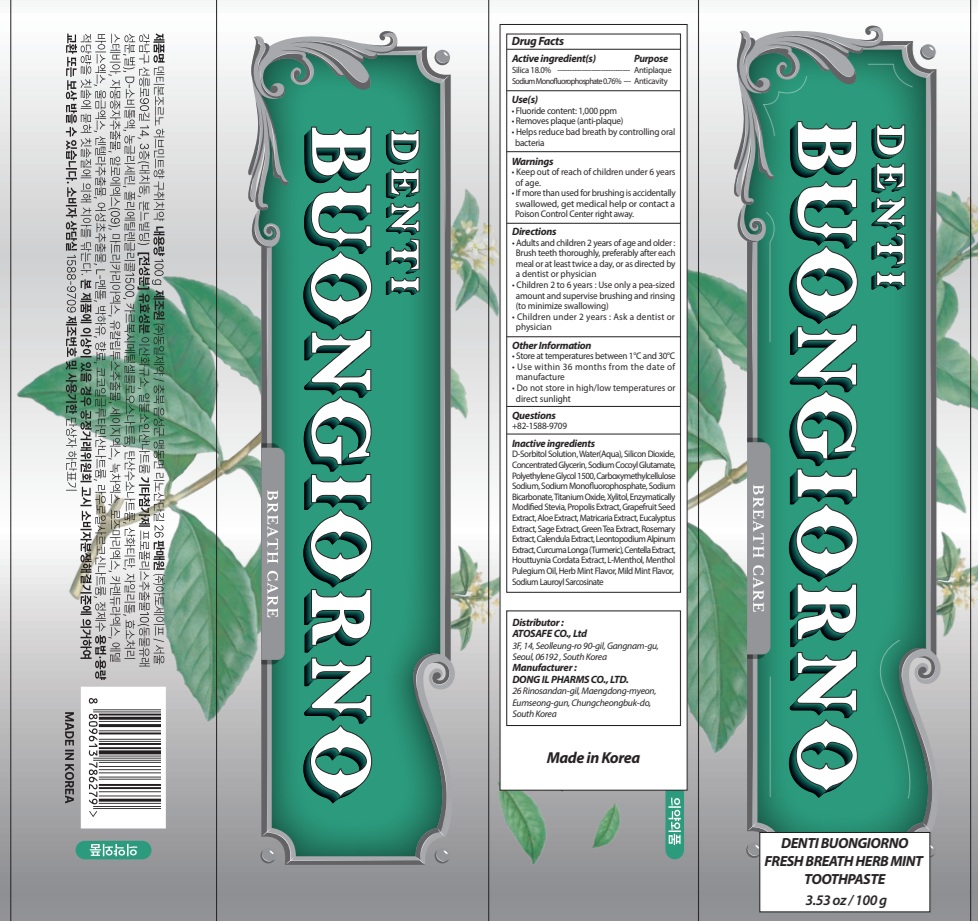 DRUG LABEL: DENTI BUONGIORNO FRESH BREATH HERB MINT TOOTH
NDC: 73242-1128 | Form: PASTE, DENTIFRICE
Manufacturer: DONG IL PHARMS CO.,LTD
Category: otc | Type: HUMAN OTC DRUG LABEL
Date: 20260116

ACTIVE INGREDIENTS: SILICON DIOXIDE 18 g/100 g; SODIUM MONOFLUOROPHOSPHATE 0.76 g/100 g
INACTIVE INGREDIENTS: SORBITOL; WATER; GLYCERIN

DENTI BUONGIORNO FRESH BREATH HERB MINT TOOTHPASTE

Active ingredient(s)

Silica 18.0%

Sodium Monofluorophosphate 0.76%

Purpose

Antiplaque, Anticavity

Warnings

• Keep out of reach of children under 6 years of age.
• If more than used for brushing is accidentally swallowed, get medical help or contact a Poison Control Center right away.

KEEP OUT OF REACH OF CHILDREN

Keep out of reach of childrenunder 6 years of age.

INDICATIONS AND USAGE

Use(s)

• Helps remove plaque and tartar buildup
• Helps prevent cavities
• Helps reduce gum inflammation and promote healthy teeth

Directions

• Adults and children 2 years of age and older : Brush teeth thoroughly, preferably after each meal or at least twice a day, or as directed by a dentist or physician

• Children 2 to 6 years : Use only a pea sized amount and supervise child's brushing and rinsing (to minimize swallowing)

• Children under 2 years : Ask a dentist or physician

Other Information

• Store at temperatures between 1°C and 30°C
• Use within 36 months from the date of manufacture
• Do not store in high/low temperatures or direct sunlight

Questions

+82-1588-9709

Inactive ingredients

D-Sorbitol Solution, Water(Aqua) ,Silicon Dioxide , Concentrated Glycerin, Sodium Cocoyl Glutamate, Polyethylene Glycol 1500, Carboxymethylcellulose Sodium, Sodium Monofluorophosphate, Sodium Bicarbonate, Titanium Oxide, Xylitol, Enzymatically Modified Stevia, Propolis Extract, Grapefruit Seed Extract, Aloe Extract, Matricaria Extract, Eucalyptus Extract, Sage Extract, Green Tea Extract, Rosemary Extract, Calendula Extract, Leontopodium Alpinum Extract, Curcuma Longa (Turmeric), Centella Extract, Houttuynia Cordata Extract, L-Menthol, Menthol Pulegium Oil, Herb Mint Flavor, Mild Mint Flavor, Sodium Lauroyl Sarcosinate